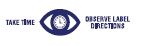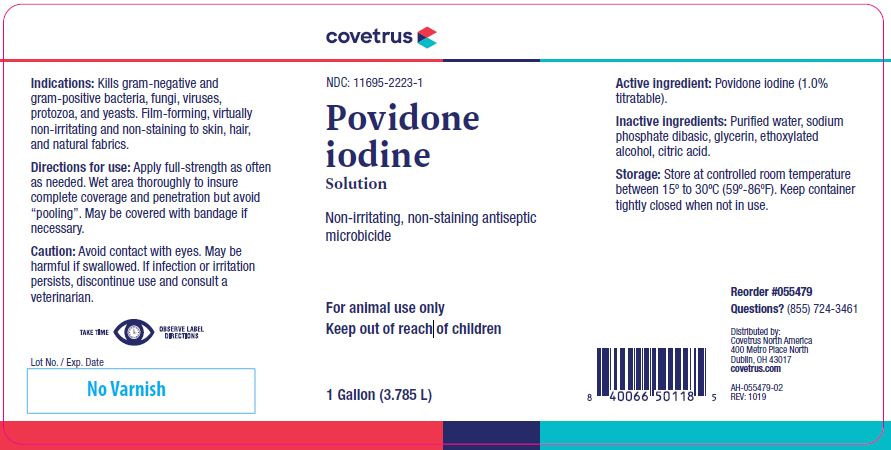 DRUG LABEL: Povidone iodine
NDC: 11695-2223 | Form: SOLUTION
Manufacturer: Butler Animal health Supply, LLC dba Covetrus North America
Category: animal | Type: OTC ANIMAL DRUG LABEL
Date: 20191120

ACTIVE INGREDIENTS: POVIDONE-IODINE 65.9 g/1 L

Povidone
iodine
Solution

VETERINARY INDICATIONS

Non-irritating, non-staining antiseptic microbicide

KEEP OUT OF REACH OF CHILDREN

For animal use only
Keep out of reach of children

HOW SUPPLIED

1 Gallon (3.785 L)

Indications:

Kills gram-negative and gram-positive bacteria, fungi, viruses, protozoa, and yeasts. Film-forming, virtually non-irritating and non-staining to skin, hair, and natural fabrics.

Directions for use:

Apply full-strength as often as needed. Wet area thoroughly to insure complete coverage and penetration but avoid “pooling”. May be covered with bandage if necessary.

Caution:

Avoid contact with eyes. May be harmful if swallowed. If infection or irritation persists, discontinue use and consult a veterinarian.

Active ingredient:

Povidone iodine (1.0% titratable).

Inactive ingredients:

Purified water, sodium phosphate dibasic, glycerin, ethoxylated alcohol, citric acid.

Storage:

Store at controlled room temperature between 15º to 30ºC (59º-86ºF). Keep container tightly closed when not in use.

INFORMATION FOR OWNERS/CAREGIVERS

Reorder #055479
Questions? (855) 724-3461
Distributed by:
Covetrus North America
400 Metro Place North
Dublin, OH 43017
covetrus.com

AH-055479-02
REV: 1019